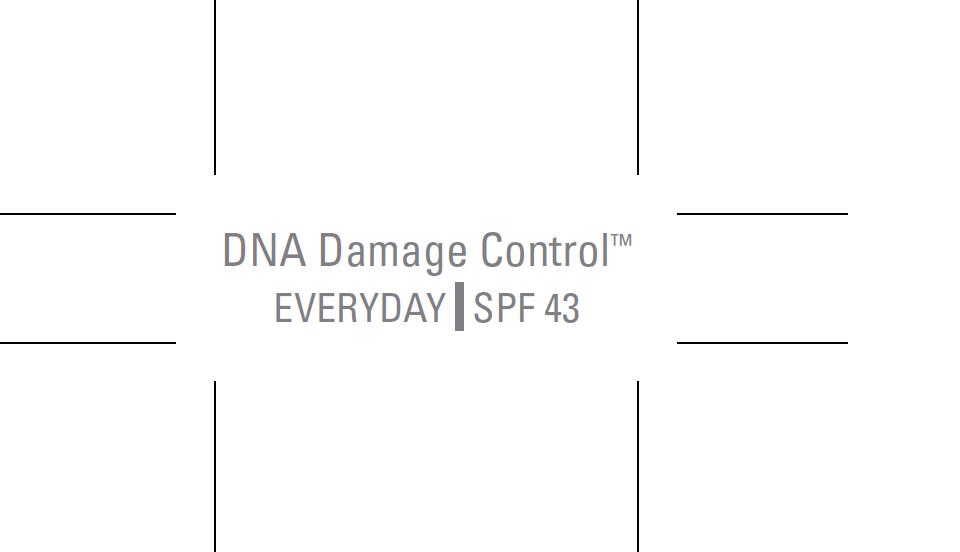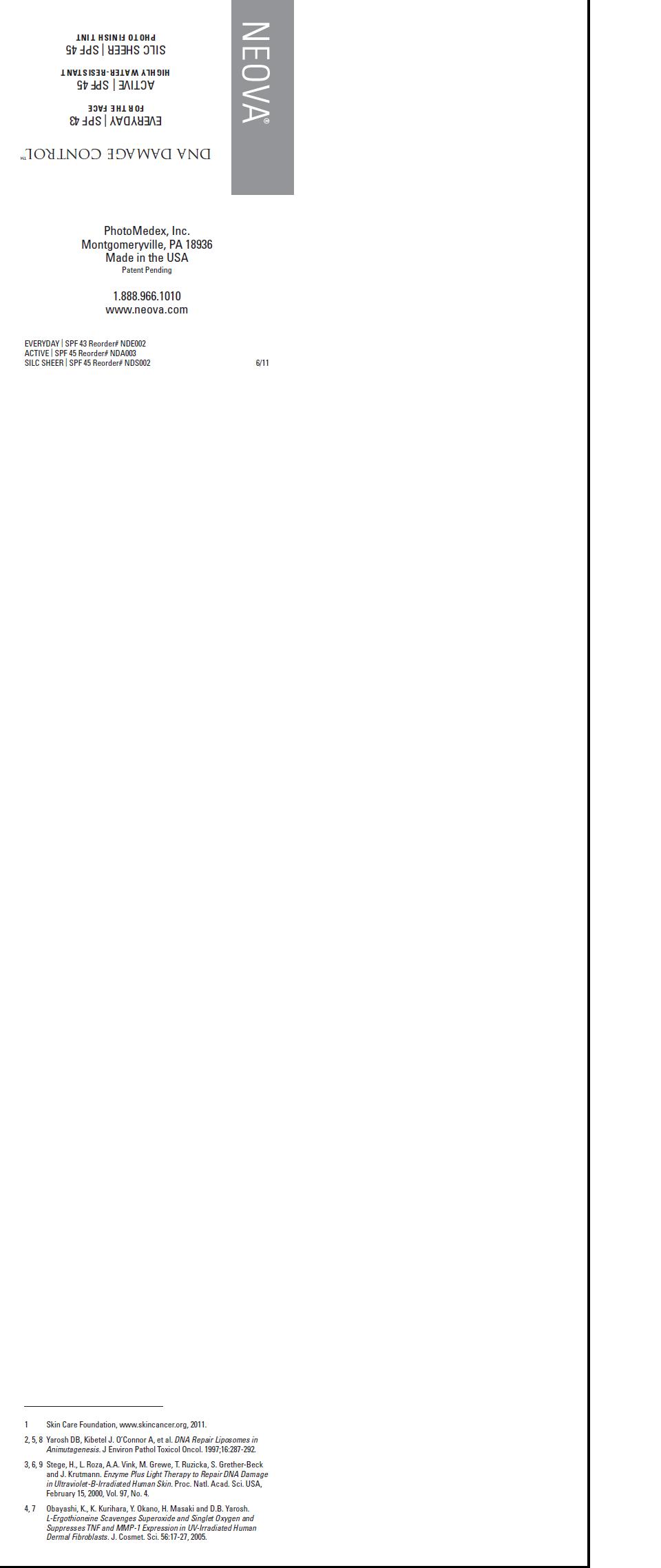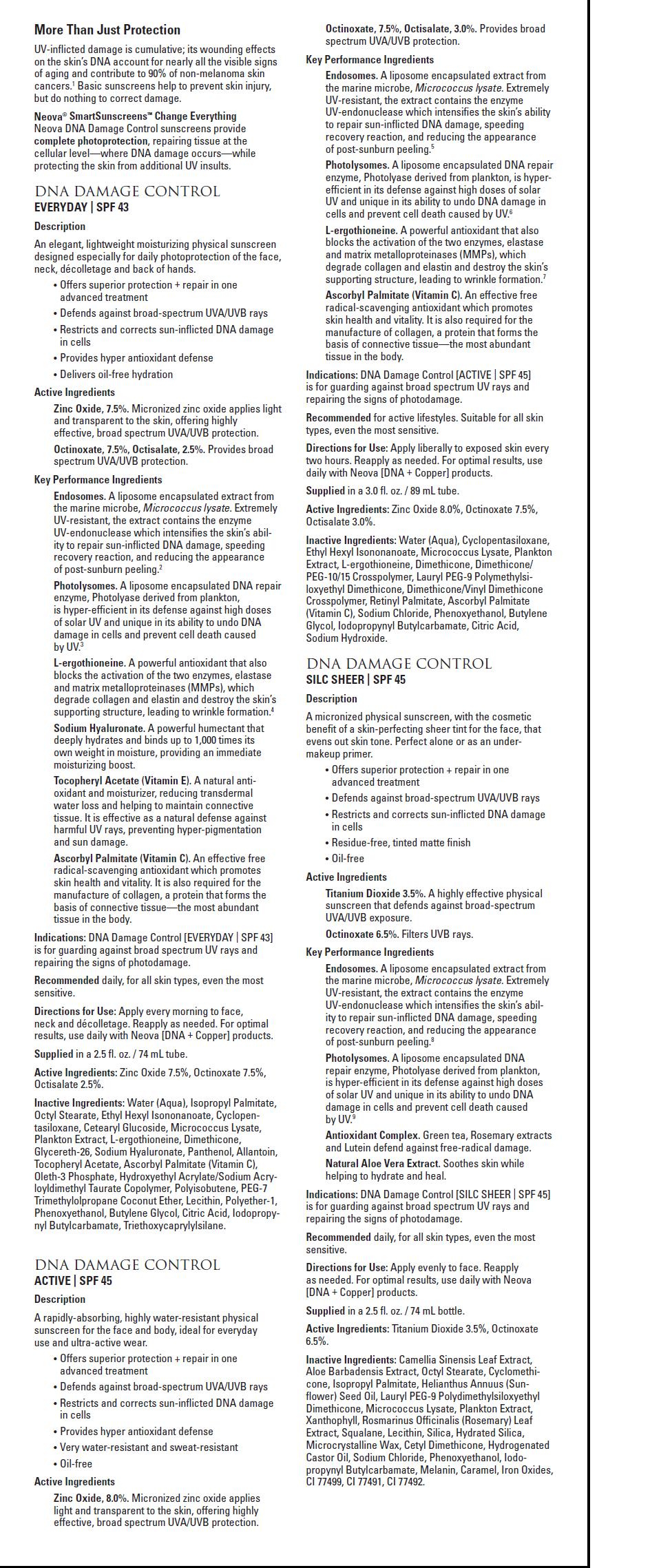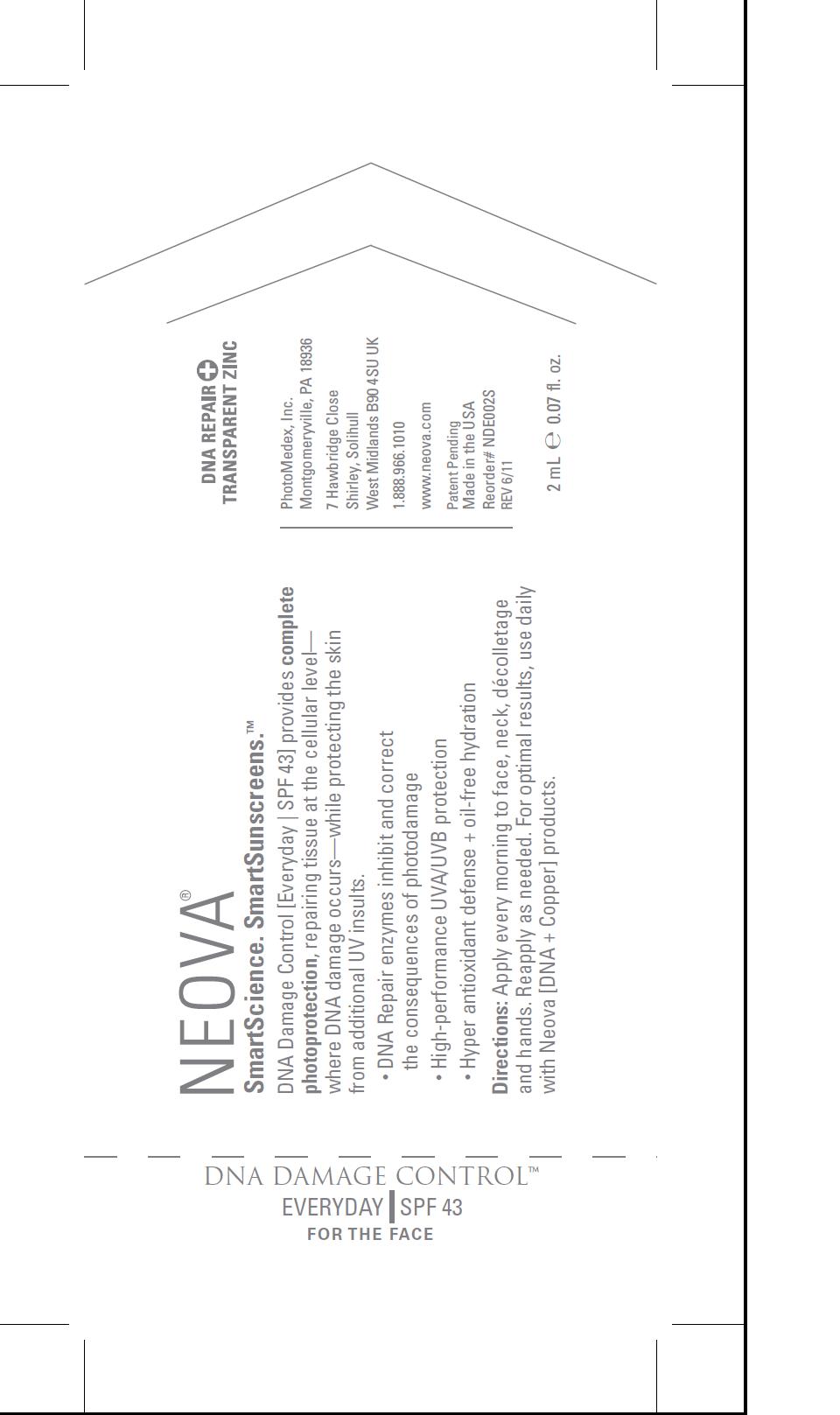 DRUG LABEL: Neova DNA Damage Control - Everyday
NDC: 62362-139 | Form: EMULSION
Manufacturer: PhotoMedex, Inc.
Category: otc | Type: HUMAN OTC DRUG LABEL
Date: 20120106

ACTIVE INGREDIENTS: Zinc Oxide 7.5 mL/100 mL; Octinoxate 7.5 mL/100 mL; Octisalate 2.5 mL/100 mL
INACTIVE INGREDIENTS: Water; Isopropyl Palmitate; Octyl Stearate; Ethylhexyl Isononanoate; Cyclomethicone 5; Cetearyl Glucoside; Ergothioneine; Dimethicone; Glycereth-26; Hyaluronate Sodium ; Panthenol; Allantoin; Alpha-Tocopherol Acetate; Ascorbyl Palmitate; Oleth-3 Phosphate; Polyisobutylene (1300 MW); Egg Phospholipids; Butylene Glycol; Citric Acid; Iodopropynyl Butylcarbamate; Triethoxycaprylylsilane

Neova DNA Damage Control - Everyday SPF 43 - 2mL sample package insert

Directions for use:

Apply every morning to face, neck, décolletage
and hands. Reapply as needed. For optimal results, use daily
with Neova [DNA + Copper] products.

Supplied

in a 2.5 fl. oz. / 74 mL tube.

Active Ingredients:

Zinc Oxide 7.5%, Octinoxate 7.5%, Octisalate 2.5%.

Inactive Ingredients:

Water (Aqua), Isopropyl Palmitate,
Octyl Stearate, Ethyl Hexyl Isononanoate, Cyclopentasiloxane,
Cetearyl Glucoside, Micrococcus Lysate,
Plankton Extract, L-ergothioneine, Dimethicone,
Glycereth-26, Sodium Hyaluronate, Panthenol, Allantoin,
Tocopheryl Acetate, Ascorbyl Palmitate (Vitamin C),
Oleth-3 Phosphate, Hydroxyethyl Acrylate/Sodium Acryloyldimethyl
Taurate Copolymer, Polyisobutene, PEG-7
Trimethylolpropane Coconut Ether, Lecithin, Polyether-1,
Phenoxyethanol, Butylene Glycol, Citric Acid, Iodopropynyl
Butylcarbamate, Triethoxycaprylylsilane.

Image of package insert, package, and pouch

PkgInsertUniversalpg1.jpg PkgInsertUniversalpg2.jpg AmpuleEday.jpg PouchEday.jpg